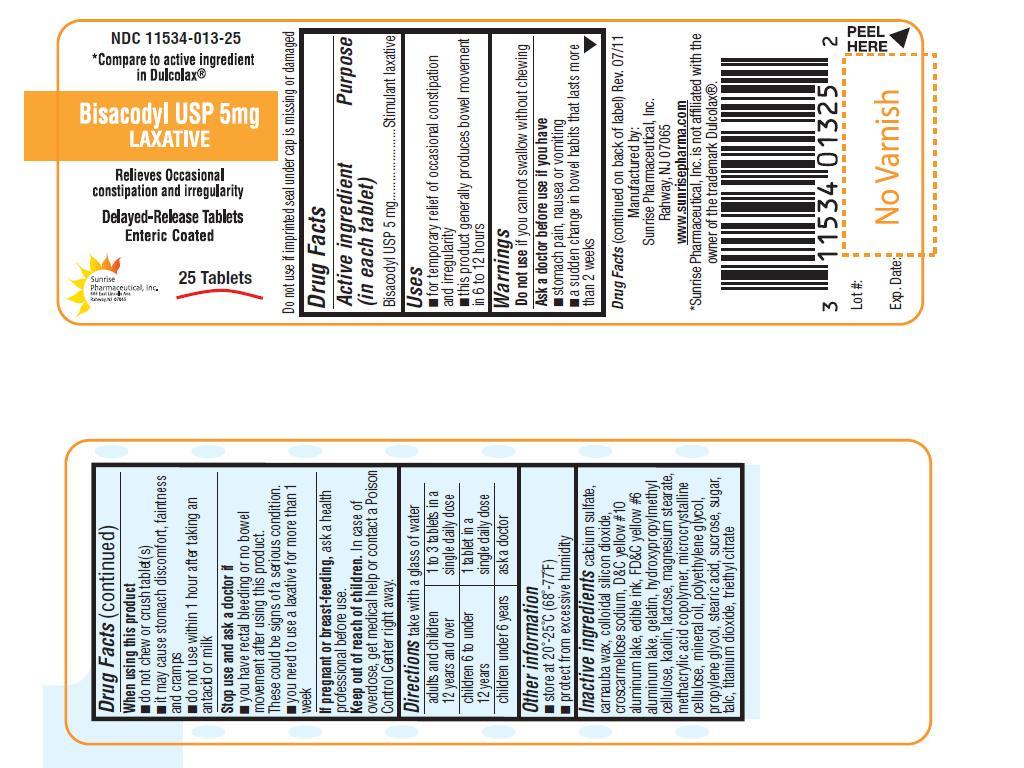 DRUG LABEL: Bisacodyl
NDC: 11534-013 | Form: TABLET, DELAYED RELEASE
Manufacturer: Sunrise Pharmaceutical Inc
Category: otc | Type: HUMAN OTC DRUG LABEL
Date: 20110809

ACTIVE INGREDIENTS: BISACODYL 5 mg/1 1
INACTIVE INGREDIENTS: CALCIUM SULFATE; CARNAUBA WAX; SILICON DIOXIDE; CROSCARMELLOSE SODIUM; D&C YELLOW NO. 10; FD&C YELLOW NO. 6; GELATIN; HYPROMELLOSE 2910 (5 MPA.S); KAOLIN; LACTOSE; MAGNESIUM STEARATE; METHACRYLIC ACID - ETHYL ACRYLATE COPOLYMER (1:1) TYPE A; CELLULOSE, MICROCRYSTALLINE; MINERAL OIL; POLYETHYLENE GLYCOL; PROPYLENE GLYCOL; STEARIC ACID; SUCROSE; TALC; TITANIUM DIOXIDE; TRIETHYL CITRATE

Bisacodyl USP 5 mg Laxative

ACTIVE INGREDIENT

Bisacodyl USP 5mg.

PURPOSE

Stimulant laxative.

INDICATIONS AND USAGE

For temporary relief of occasional constipation and irregularity

This product generally produces bowel movement in 6 to 12 hours.

WARNINGS

Do not use if you cannot swallow without chewing.

ASK DOCTOR BEFORE USE IF YOU HAVE

Stomach pain, nausea or vomiting

A sudden change in bowel habits that lasts for more than 2 weeks.

WHEN USING THIS PRODUCT

Do not chew or crush tablet(s).

It may cause stomach discomfort, faintness and cramps.

Do not use within 1 hour after taking an antacid or milk.

STOP USE AND ASK A DOCTOR IF

You have rectal bleeding or no bowel movement after using this product. These could be signs of serious condition.

You need to use laxative for more than 1 week

IF PREGNANT OR BREAST FEEDING

Ask a health professional before use.

Dosage and Administration text

KEEP OUT OF REACH OF CHILDREN

In case of overdose, get medical help or contact a Poison Control Center right away.

DIRECTIONS

Take with a glass of water

Adults and children 12 years and over | 1 to 3 tablets in a single daily dose
Children 6 to under 12 years | 1 tablet in a single daily dose
Children under 6 years | Ask a doctor

OTHER INFORMATION

Store at 20°-25°C(68°-77°F)

INACTIVE INGREDIENT

Calcium sulfate, carnuba wax, colloidal silicon dioxide, croscarmellose sodium, D & C yellow # 10, edible ink, FD & C yellow #6, gelatin, hydroxypropylymethyl cellulose, kaolin, lactose, magnesium stearate, methacrylic acid copolymer, microcrystalline celloluse, mineral oil, polyethylene glycol, propylene glycol, stearic acid, sucrose, sugar, talc, titanium dioxide, triethyl citrate.